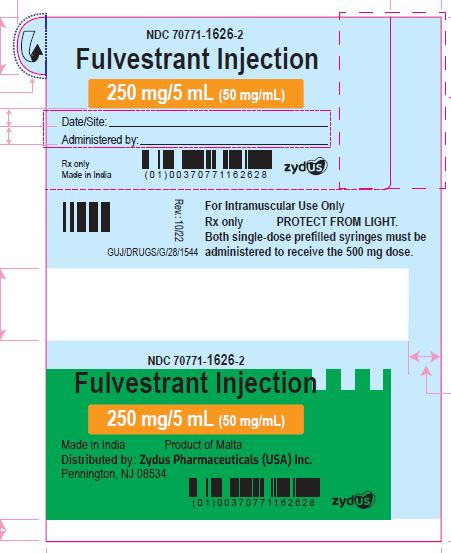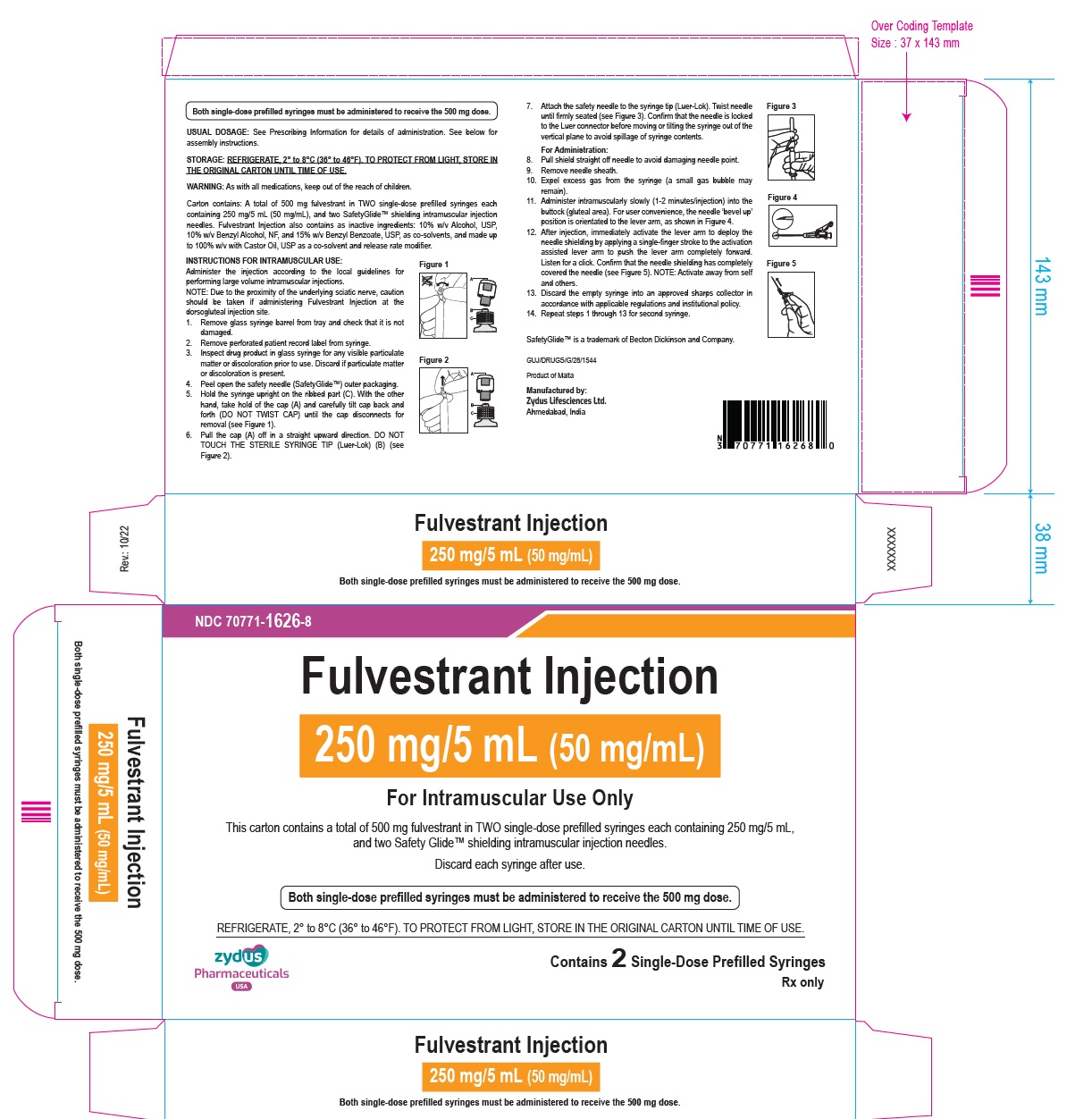 DRUG LABEL: FULVESTRANT
NDC: 70771-1626 | Form: INJECTION, SOLUTION
Manufacturer: Zydus Lifesciences Limited
Category: prescription | Type: HUMAN PRESCRIPTION DRUG LABEL
Date: 20220826

ACTIVE INGREDIENTS: FULVESTRANT 50 mg/1 mL
INACTIVE INGREDIENTS: ALCOHOL; BENZYL ALCOHOL; BENZYL BENZOATE; CASTOR OIL

Fulvestrant Injection

PACKAGE LABEL.PRINCIPAL DISPLAY PANEL

NDC 70771-1626-2

Fulvestrant Injection

250 mg/5 mL (50 mg/mL)

For Intramuscular Use Only

Both single-dose prefilled syringes must be administered to receive the 500 mg dose.

PROTECT FROM LIGHT

Rx only

Made in India

NDC 70771-1626-8

Fulvestrant Injection

250 mg/5 mL (50 mg/mL)

For Intramuscular Use Only

This carton contains a total of 500 mg fulvestrant in TWO single-dose prefilled syringes each containing 250 mg/5 mL, and two Safety Glide™ shielding intramuscular injection needles.

Discard each syringe after use.

Both single-dose prefilled syringes must be administered to receive the 500 mg dose.

STORAGE: REFRIGERATE 2° to 8°C (36° to 46°F). TO PROTECT FROM LIGHT, STORE IN THE ORIGINAL CARTON UNTIL TIME OF USE.

Contains 2 Single-Dose Prefilled Syringes

Rx only